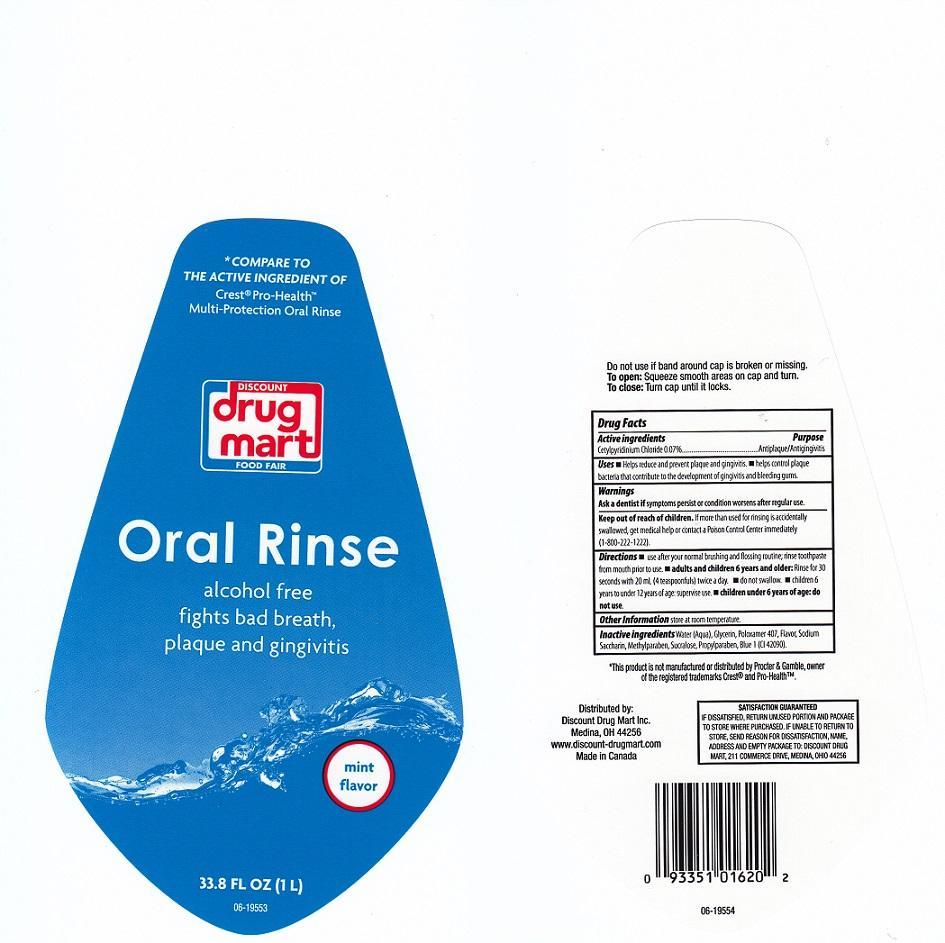 DRUG LABEL: DISCOUNT DRUG MART
NDC: 53943-553 | Form: LIQUID
Manufacturer: DISCOUNT DRUG MART
Category: otc | Type: HUMAN OTC DRUG LABEL
Date: 20140507

ACTIVE INGREDIENTS: CETYLPYRIDINIUM CHLORIDE 0.7 mg/1 mL
INACTIVE INGREDIENTS: WATER; GLYCERIN; POLOXAMER 407; SACCHARIN SODIUM; METHYLPARABEN; SUCRALOSE; PROPYLPARABEN; FD&C BLUE NO. 1

DRUG FACTS

ACTIVE INGREDIENT

CETYLPYRIDINIUM CHLORIDE 0.07%

PURPOSE

ANTIPLAQUE/ANTIGINGIVITIS

USES

HELPS REDUCE AND PREVENT PLAQUE AND GINGIVITIS. HELPS CONTROL PLAQUE BACTERIA THAT CONTRIBUTE TO THE DEVELOPMENT OF GINGIVITIS AND BLEEDING GUMS

WARNINGS

ASK A DENTIST IF SYMPTOMS PERSIST OR CONDITIOIN WORSENS AFTER REGULAR USE

KEEP OUT OF REACH OF CHILDREN

IF MORE THAN USED FOR RINSING IS ACCIDENTALLY SWALLOWED, GET MEDICAL HELP OR CONTACT A POISON CONTROL CENTER IMMEDIATELY (1-800-222-1222)

DIRECTIONS

USE AFTER YOUR NORMAL BRUSHING AND FLOSSING ROUTINE; RINSE TOOTHPASTE FROM MOUTH PRIOR TO USE. ADULTS AND CHILDREN 6 YEARS AND OLDER: RINSE FOR 30 SECONDS WITH 20 ML (4 TEASPOONFULS) TWICE A DAY. DO NOT SWALLOW. CHILDREN 6 YEARS TO UNDER 12 YEARS OF AGE: SUPERVISE USE. CHILDREN UNDER 6 YEARS OF AGE: DO NOT USE.

OTHER INFORMATION

STORE AT ROOM TEMPERATURE

INACTIVE INGREDIENTS

WATER (AQUA), GLYCERIN, POLOXAMER 407, FLAVOR, SODIUM SACCHARIN, METHYLPARABEN, SUCRALOSE, PROPYLPARABEN, BLUE 1 (CI 42090)